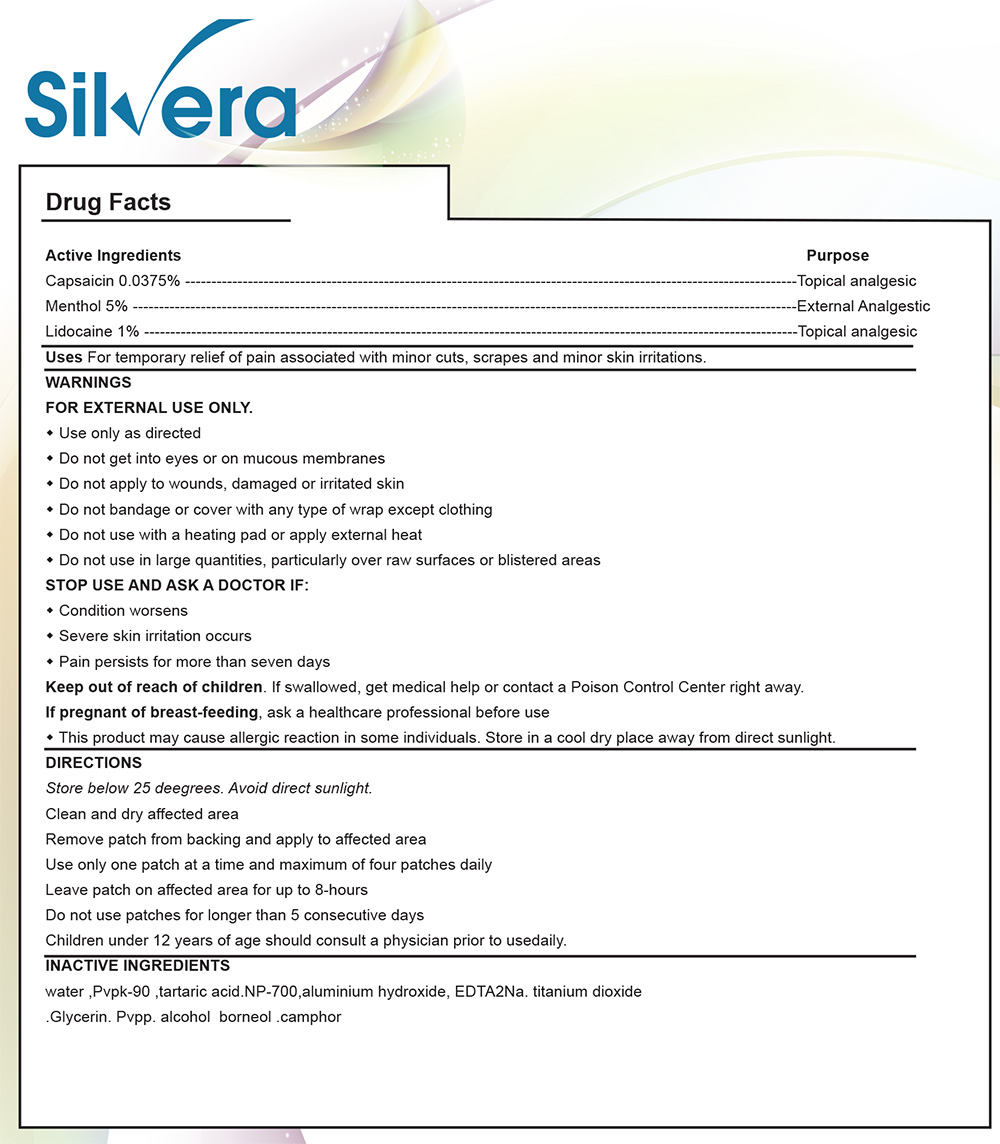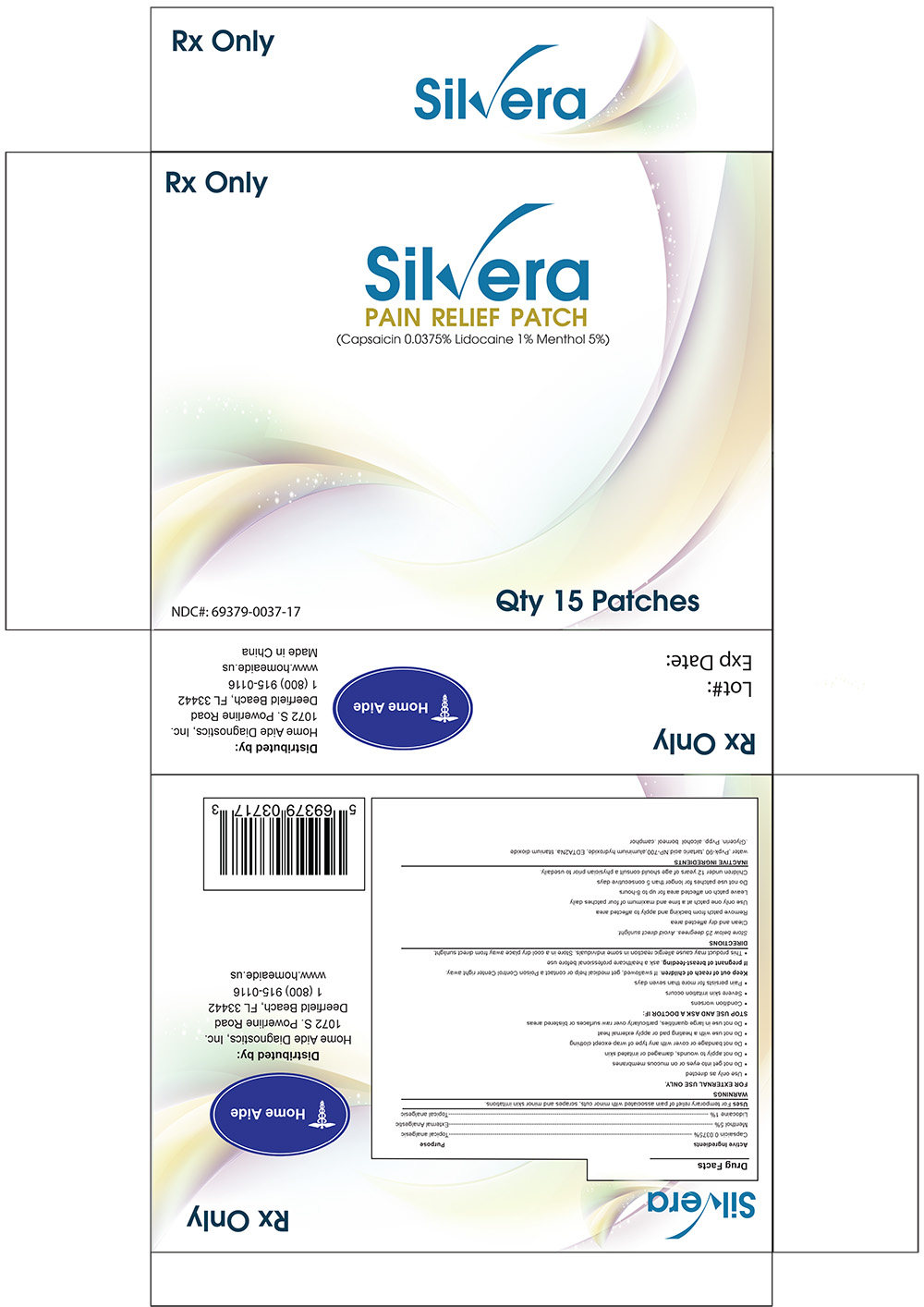 DRUG LABEL: Silvera Pain Relief Patch
NDC: 69379-037 | Form: PATCH
Manufacturer: Home Aide Diagnostics, Inc.
Category: prescription | Type: HUMAN PRESCRIPTION DRUG LABEL
Date: 20141202

ACTIVE INGREDIENTS: Lidocaine 1 g/100 g; Capsaicin .0375 g/100 g; Menthol 5 g/100 g

SILVERA PAIN RELIEF PATCH

GENERAL PRECAUTIONS

This product may cause allergic reactions in some individuals.